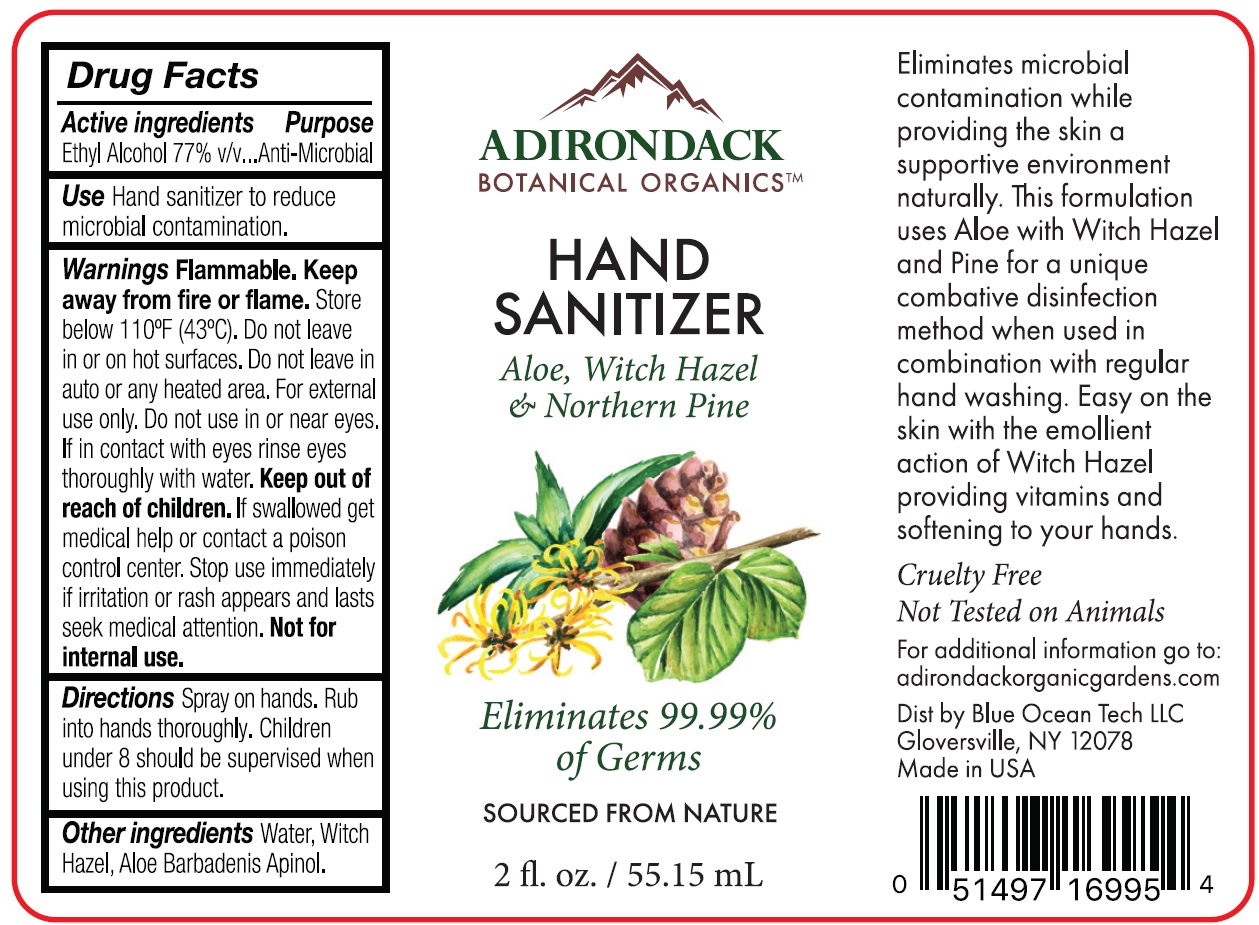 DRUG LABEL: Adirondack Botanical Organics Hand Sanitizer
NDC: 80987-000 | Form: SPRAY
Manufacturer: Blue Ocean Tech LLC
Category: otc | Type: HUMAN OTC DRUG LABEL
Date: 20201106

ACTIVE INGREDIENTS: ALCOHOL 0.77 mL/1 mL
INACTIVE INGREDIENTS: ALOE VERA WHOLE; WHITE PINE OIL; WATER; WITCH HAZEL

Adirondack Botanical Organics Hand Sanitizer

Active ingredients

Ethyl Alcohol 77% v/v

Purpose

Anti-Microbial

Use

Hand sanitizer to reduce microbial contamination.

Warnings

Flammable. Keep away from fire or flame. Store below 110°F (43°C). Do not leave in or on hot surfaces. Do not leave in auto or any heated area. For external use only.

Do not use

in or near eyes. If in contact with eyes rinse eyes thoroughly with water.

Keep out of reach of children.

If swallowed, get medical help or contact a poison control center.

Stop use

immediately if irritation or rash appears and lasts seek medical attention. Not for internal use.

Directions

Spray on hands. Rub into hands thoroughly. Children under 8 should be supervised when uing this product.

Other ingredients

Water, Witch Hazel, Aloe Barbadenis Apinol.